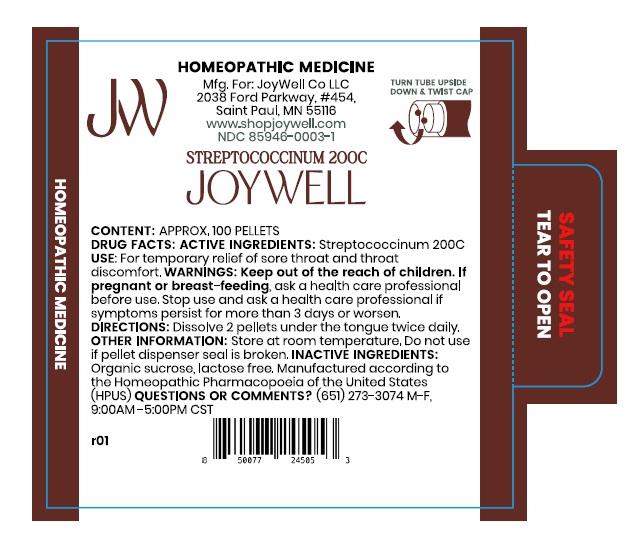 DRUG LABEL: Streptococcinum 200C
NDC: 85946-0003 | Form: PELLET
Manufacturer: JoyWell Co LLC
Category: homeopathic | Type: HUMAN OTC DRUG LABEL
Date: 20251211

ACTIVE INGREDIENTS: STREPTOCOCCUS PYOGENES 200 [hp_C]/1 1
INACTIVE INGREDIENTS: SUCROSE

Active ingredients

Streptococcinum 200C

Uses

For temporary relief of sore throat and throat discomfort.

Warnings

Keep out of the reach of children. If pregnant or breast-feeding, ask a health care professional before use.

Stop use and ask a health care professional if symptoms persist for more than 3 days or worsen.

Directions

Dissolve 2 pellets under the tongue twice daily.

Other informmation

Store at room temperature. Do not use if pellet dispenser seal is broken.

Inactive ingredients

Organic sucrose

Lactose-free Manufactured according to the Homeopathic Pharmacopoeia of the United States (HPUS).

QUESTIONS OR COMMENTS?

(651) 273-3074 M-F, 9:00AM -5:00PM CST